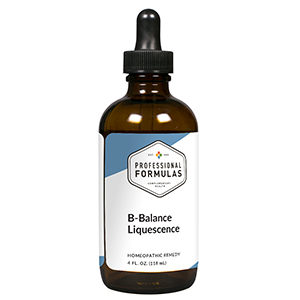 DRUG LABEL: B-Balance Liquescence
NDC: 63083-3003 | Form: LIQUID
Manufacturer: Professional Complementary Health Formulas
Category: homeopathic | Type: HUMAN OTC DRUG LABEL
Date: 20190815

ACTIVE INGREDIENTS: LATIGLUTENASE 2 [hp_X]/118 mL; YEAST, UNSPECIFIED 2 [hp_X]/118 mL; NIACIN 3 [hp_X]/118 mL; PANTOTHENIC ACID 3 [hp_X]/118 mL; THIAMINE 4 [hp_X]/118 mL; CYANOCOBALAMIN 4 [hp_X]/118 mL; BEEF HEART 6 [hp_X]/118 mL; BEEF LIVER 6 [hp_X]/118 mL; RIBOFLAVIN 6 [hp_X]/118 mL; PYRIDOXINE 6 [hp_X]/118 mL
INACTIVE INGREDIENTS: ALCOHOL; WATER

T3

ACTIVE INGREDIENTS

Hordeum vulgare 2X
Saccharomyces 2X
Vitamin B3 3X
Vitamin B5 3X
Vitamin B1 4X
Vitamin B12 4X
Heart 6X
Liver 6X
Vitamin B2 6X
Vitamin B6 6X

QUESTIONS

Professional Formulas

PO Box 2034 Lake Oswego, OR 97035

INDICATIONS

For the temporary relief of anxiousness, difficulty concentrating, irritability, sadness, dry or irritated skin, difficulty falling asleep or restlessness, or occasional headache.*

PURPOSE

*Claims based on traditional homeopathic practice, not accepted medical evidence. Not FDA evaluated.

WARNINGS

In case of overdose, get medical help or contact a poison control center right away.

Keep out of the reach of children.

PREGNANCY OR BREAST FEEDING

If pregnant or breastfeeding, ask a healthcare professional before use.

DIRECTIONS

Place drops under tongue 30 minutes before/after meals. Adults and children 12 years and over: Take one full dropper up to 2 times per day. Consult a physician for use in children under 12 years of age.

OTHER INFORMATION

Tamper resistant. If seal is broken, do not use. After opening, close container tightly and store at room temperature away from heat.

INACTIVE INGREDIENTS

20% ethanol, purified water.

LABEL

Est 1985

Professional Formulas

Complementary Health

B-Balance Liquescence

Homeopathic Remedy

4 FL. OZ. (118 mL)